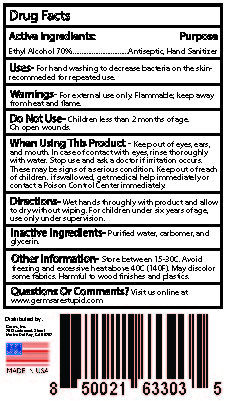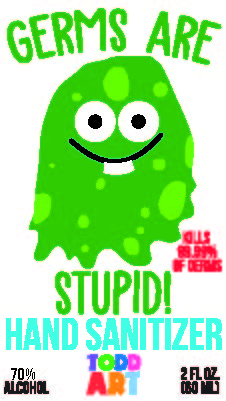 DRUG LABEL: Germs Are Stupid
NDC: 81821-001 | Form: GEL
Manufacturer: Germs, Inc.
Category: otc | Type: HUMAN OTC DRUG LABEL
Date: 20210414

ACTIVE INGREDIENTS: ALCOHOL 70 mL/100 mL
INACTIVE INGREDIENTS: GLYCERIN 1.45 mL/100 mL; WATER; METHACRYLIC ACID - ETHYL ACRYLATE COPOLYMER (4500 MPA.S) 4 mL/100 mL

70 No Scent Gel

This is a hand sanitizer manufactured according to the Temporary Policy for Preparation of Certain Alcohol-Based Hand Sanitizer Products During the Public Health Emergency (CoViD-19); Guidance for Industry.

The hand sanitizer is manufactured using only the following United States Pharmacopoeia (USP) grade ingredients in the preparation of the product (percentage in final product formulation) consistent with World Health Organization (WHO) recommendations:

1. Alcohol (ethanol) (USP or Food Chemical Codex (FCC) grade) (70%, volume/volume (v/v)) in an aqueous solution denatured according to Alcohol and Tobacco Tax and Trade Bureau regulations in 27 CFR part 20.
2. Glycerol (1.45% v/v).
3. Hydrogen peroxide (0.125% v/v).
4. Sterile distilled water or boiled cold water.
5. Carbomer

Active Ingredient(s)

Alcohol 70% v/v. Purpose: Antiseptic

Purpose

Antiseptic, Hand Sanitizer

Use

For hand washing to decrease bacteria on the skin - Recommended for repeated use.

Warnings

For external use only. Flammable. Keep away from heat or flame

Do not use

- in children less than 2 months of age
- on open skin wounds

When using this product keep out of eyes, ears, and mouth. In case of contact with eyes, rinse eyes thoroughly with water.
Stop use and ask a doctor if irritation occurs. These may be signs of a serious condition.
Keep out of reach of children. If swallowed, get medical help immediately or contact a Poison Control Center immediately.

Stop use and ask a doctor if irritation or rash occurs. These may be signs of a serious condition.

Keep out of reach of children. If swallowed, get medical help or contact a Poison Control Center right away.

Directions

Wet hands thoroughly with product, and allow to dry without wiping. For children under six, use only under adult supervision.

Other information

- Store between 15-30C (59-86F)
- Avoid freezing and excessive heat above 40C (104F)
- May discolor some fabrics. Harmful to wood finishes and plastics

Inactive ingredients

glycerin,carbomer, and purified water USP